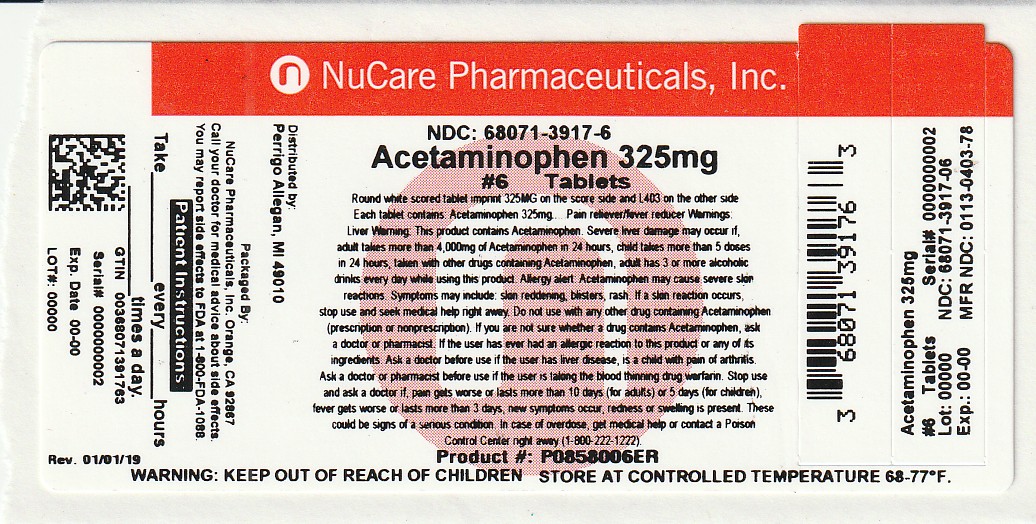 DRUG LABEL: good sense pain relief
NDC: 68071-3917 | Form: TABLET
Manufacturer: NuCare Pharamceuticals, Inc.
Category: otc | Type: HUMAN OTC DRUG LABEL
Date: 20251120

ACTIVE INGREDIENTS: ACETAMINOPHEN 325 mg/1 1
INACTIVE INGREDIENTS: CROSCARMELLOSE SODIUM; POVIDONE, UNSPECIFIED; STEARIC ACID

Perrigo Pain Relief Tablets Drug Facts

Active ingredient (in each tablet)

Acetaminophen 325 mg

Purpose

Pain reliever/fever reducer

Uses

1. temporarily relieves minor aches and pains due to:
2. the common cold
3. headache
4. minor pain of arthritis
5. backache
6. muscular aches
7. toothache
8. premenstrual and menstrual cramps
9. temporarily reduces fever

Warnings

Liver warning:This product contains acetaminophen. Severe liver damage may occur if

- adult takes more than 4,000 mg of acetaminophen in 24 hours
- child takes more than 5 doses in 24 hours
- taken with other drugs containing acetaminophen
- adult has 3 or more alcoholic drinks every day while using this product

Allergy alert:Acetaminophen may cause severe skin reactions. Symptoms may include:

- skin reddening
- blisters
- rash

If a skin reaction occurs, stop use and seek medical help right away.

Do not use

- with any other drug containing acetaminophen (prescription or nonprescription). If you are not sure whether a drug contains acetaminophen, ask a doctor or pharmacist.
- if the user has ever had an allergic reaction to this product or any of its ingredients

Ask a doctor before use if the user

1. has liver disease
2. is a child with pain of arthritis

Ask a doctor or pharmacist before use if the user is

taking the blood thinning drug warfarin

Stop use and ask a doctor if

1. new symptoms occur
2. pain gets worse or lasts more than 10 days (for adults) or 5 days (for children)
3. fever gets worse or lasts more than 3 days
4. redness or swelling is present

These could be signs of a serious condition.

If pregnant or breast-feeding,

ask a health professional before use.

Keep out of reach of children.

Overdose warning:In case of overdose, get medical help or contact a Poison Control Center right away (1-800-222-1222). Quick medical attention is critical for adults as well as for children even if you do not notice any signs or symptoms.

Directions

- do not take more than directed (see overdose warning)

 | adults and children 12 years and over | - take 2 tablets every 4 to 6 hours while symptoms last - do not take more than 10 tablets in 24 hours - do not use for more than 10 days unless directed by a doctor
 | children; 6-11 years | - take 1 tablet every 4 to 6 hours while symptoms last - do not take more than 5 tablets in 24 hours - do not use for more than 5 days unless directed by a - doctor
 | children under; 6 years | ask a doctor

Inactive ingredients

croscarmellose sodium*, povidone, pregelatinized starch, stearic acid *may contain this ingredient

Questions or comments?

1-800-719-9260